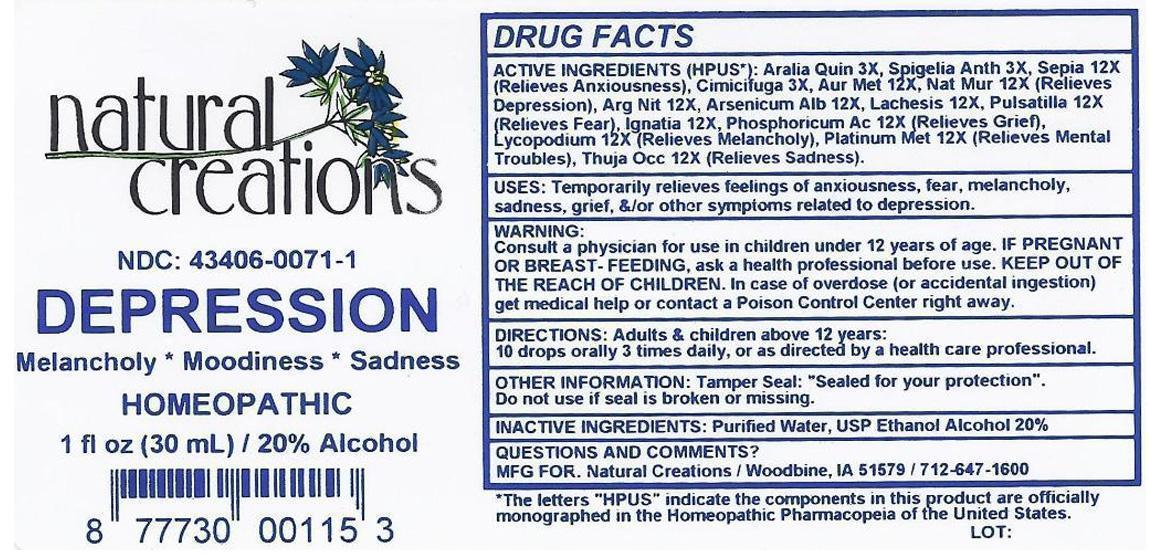 DRUG LABEL: DEPRESSION
NDC: 43406-0071 | Form: LIQUID
Manufacturer: Natural Creations, Inc.
Category: homeopathic | Type: HUMAN OTC DRUG LABEL
Date: 20130122

ACTIVE INGREDIENTS: AMERICAN GINSENG 3 [hp_X]/1 mL; BLACK COHOSH 3 [hp_X]/1 mL; SPIGELIA ANTHELMIA 3 [hp_X]/1 mL; SILVER NITRATE 12 [hp_X]/1 mL; ARSENIC TRIOXIDE 12 [hp_X]/1 mL; GOLD 12 [hp_X]/1 mL; STRYCHNOS IGNATII SEED 12 [hp_X]/1 mL; LACHESIS MUTA VENOM 12 [hp_X]/1 mL; LYCOPODIUM CLAVATUM SPORE 12 [hp_X]/1 mL; SODIUM CHLORIDE 12 [hp_X]/1 mL; PHOSPHORIC ACID 12 [hp_X]/1 mL; PLATINUM 12 [hp_X]/1 mL; PULSATILLA VULGARIS 12 [hp_X]/1 mL; SEPIA OFFICINALIS JUICE 12 [hp_X]/1 mL; THUJA OCCIDENTALIS LEAFY TWIG 12 [hp_X]/1 mL
INACTIVE INGREDIENTS: WATER; ALCOHOL

DEPRESSION

ACTIVE INGREDIENT

ACTIVE INGREDIENTS (HPUS*): Aralia Quinquefolia 3X, Cimicifuga Racemosa 3X, Spigelia Anthelmintica 3X, Argentum Nitricum 12X, Arsenicum Album 12X, Aurum Metallicum 12X, Igantia Amara 12X, Lachesis Mutus 12X, Lycopodium Clavatum 12X, Natrum Muriaticum 12X, Phosphoricum Acidum 12X, Platinum Metallicum 12X, Pulsatilla 12X, Sepia 12X, Thuja Occidentalis 12X

PURPOSE

USES: Temporarily relieves feelings of anxiousness, fear, melancholy, sadness, grief, &/or other symptoms related to depression.

KEEP OUT OF REACH OF CHILDREN

KEEP OF THE REACH OF CHILDREN. In case of overdose (or accidental ingestion) get medical help or contact a Poison Control Center.

INDICATIONS AND USAGE

USES: Temporarily relieves feelings of anxiousness, fear, melancholy, sadness, grief, &/or other symptoms related to depression.

WARNING:

Consult a physician for use in children under 12 years of age. IF PREGNANT OR BREAST-FEEDING, ask a health professional before use. KEEP OUT OF THE REACH OF CHILDREN. In case of overdose (or accidental ingestion) get medical help or contact a Poison Control Center right away.

DOSAGE AND ADMINISTRATION

DIRECTIONS: Adults & children above 12 years:

10 drops orally 3 times daily, or as directed by a health care professional.

INACTIVE INGREDIENTS: Purified Water, USP Ethanol Alcohol 20%

PACKAGE LABEL

NDC: 43406-0071-1

DEPRESSION

Melancholy*Moodiness*Sadness

HOMEOPATHIC

1 fl oz (30 mL) / 20% Alcohol

UPC: 877730001153